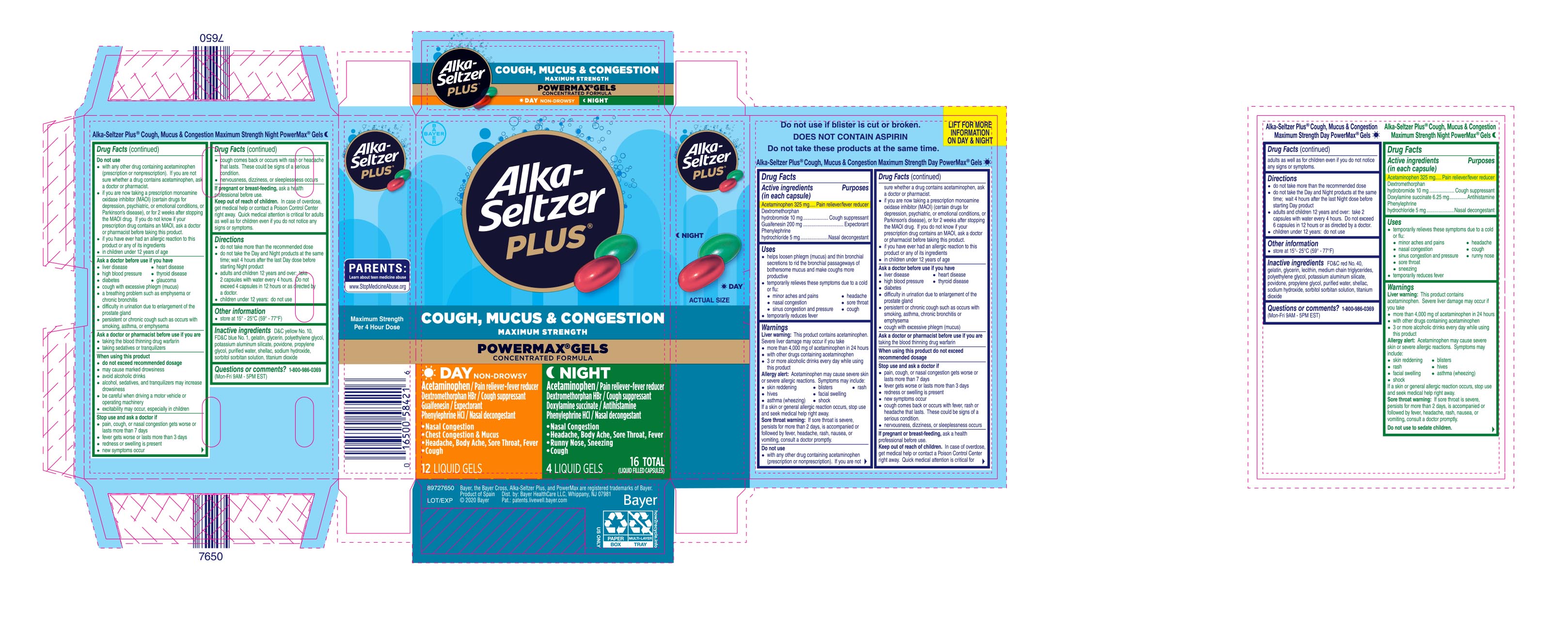 DRUG LABEL: Alka-Seltzer Plus Maximum Strength Cough, Mucus and Congestion Day and Night
NDC: 0280-0062 | Form: KIT | Route: ORAL
Manufacturer: Bayer HealthCare, LLC.
Category: otc | Type: HUMAN OTC DRUG LABEL
Date: 20251204

ACTIVE INGREDIENTS: GUAIFENESIN 200 mg/1 1; ACETAMINOPHEN 325 mg/1 1; PHENYLEPHRINE HYDROCHLORIDE 5 mg/1 1; DEXTROMETHORPHAN HYDROBROMIDE 10 mg/1 1; DEXTROMETHORPHAN HYDROBROMIDE 10 mg/1 1; PHENYLEPHRINE HYDROCHLORIDE 5 mg/1 1; ACETAMINOPHEN 325 mg/1 1; DOXYLAMINE SUCCINATE 6.25 mg/1 1
INACTIVE INGREDIENTS: POLYETHYLENE GLYCOL, UNSPECIFIED; PROPYLENE GLYCOL; SODIUM HYDROXIDE; GELATIN; MEDIUM-CHAIN TRIGLYCERIDES; POVIDONE; WATER; SHELLAC; SORBITAN; SORBITOL; TITANIUM DIOXIDE; FD&C RED NO. 40; LECITHIN, SOYBEAN; POTASSIUM ALUMINUM DISILICATE; D&C YELLOW NO. 10; GELATIN; POLYETHYLENE GLYCOL, UNSPECIFIED; SORBITOL; FD&C BLUE NO. 1; POVIDONE; SHELLAC; SODIUM HYDROXIDE; SORBITAN; TITANIUM DIOXIDE; PROPYLENE GLYCOL; POTASSIUM ALUMINUM DISILICATE; WATER

Alka-Seltzer Plus Maximum Strength Cough, Mucus and Congestion Powermax Day and Night Liquigels UI 1614294 and 1613941

Drug Facts

Do not take these products at the same time.

Alka-Seltzer Plus® Maximum Strength Cough, Mucus & Congestion Day PowerMax® Gels

Active ingredients

Active ingredients (in each capsule) Purposes

Acetaminophen 325 mg…………….……….Pain reliever/fever reducer

Dextromethorphan hydrobromide 10 mg…………..Cough suppressant

Guaifenesin 200 mg…………………………………………..Expectorant

Phenylephrine hydrochloride 5 mg………………...Nasal decongestant

Uses

· helps loosen phlegm (mucus) and thin bronchial secretions to rid

the bronchial passageways of bothersome mucus and make coughs

more productive

· temporarily relieves these symptoms due to a cold or flu:

· nasal congestion · sinus congestion and pressure

· minor aches and pains · headache

· cough · sore throat

· temporarily reduces fever

Warnings

Liver warning: This product contains acetaminophen. Severe liver damage may occur if you take

· more than 4,000 mg of acetaminophen in 24 hours

· with other drugs containing acetaminophen

· 3 or more alcoholic drinks every day while using this product

Allergy alert: Acetaminophen may cause severe skin or severe

allergic reactions. Symptoms may include:

· skin reddening · blisters · rash · hives

· facial swelling · asthma (wheezing) · shock

If a skin or general allergic reaction occurs, stop use and seek medical help right away.

Sore throat warning: If sore throat is severe, persists for more than

2 days, is accompanied or followed by fever, headache, rash, nausea,

or vomiting, consult a doctor promptly.

Do not use

● with any other drug containing acetaminophen (prescription or

nonprescription). If you are not sure whether a drug contains

acetaminophen, ask a doctor or pharmacist.

● if you are now taking a prescription monoamine oxidase inhibitor

(MAOI) (certain drugs for depression, psychiatric, or emotional

conditions, or Parkinson's disease), or for 2 weeks after stopping

the MAOI drug. If you do not know if your prescription drug contains

an MAOI, ask a doctor or pharmacist before taking this product.

● if you have ever had an allergic reaction to this product or any of its

ingredients

● in children under 12 years of age

Ask a doctor before use if you have

● liver disease ● heart disease ● high blood pressure

● thyroid disease ● diabetes

● difficulty in urination due to enlargement of the prostate gland

● persistent or chronic cough such as occurs with smoking, asthma,

chronic bronchitis or emphysema

● cough with excessive phlegm (mucus)

When using this product do not exceed recommended dosage

Ask a doctor or pharmacist before use if you are taking the blood thinning drug warfarin

Stop use and ask a doctor if

· pain, cough, or nasal congestion gets worse or lasts more than 7 days

· fever gets worse or lasts more than 3 days

· redness or swelling is present

· new symptoms occur

· cough comes back or occurs with fever, rash or headache that lasts.

These could be signs of a serious condition.

· nervousness, dizziness, or sleeplessness occurs

If pregnant or breast-feeding, ask a health professional before use.

Keep out of reach of children. In case of overdose, get medical help or contact a Poison Control Center right away. Quick medical attention is critical for adults as well as for children even if you do not notice any signs or symptoms.

Directions

· do not take more than the recommended dose

· do not take the Day and Night products at the same time; wait 4 hours

after the last Night dose before starting Day product

· adults and children 12 years and over: take 2 capsules with water

every 4 hours. Do not exceed 6 capsules in 12 hours or as

directed by a doctor.

· children under 12 years: do not use

Other information

· store at 15°- 25°C (59° - 77°F)

Inactive ingredients

Inactive ingredients FD&C red No. 40, gelatin, glycerin, lecithin, medium chain triglycerides, polyethylene glycol, potassium aluminum silicate, povidone, propylene glycol, purified water, shellac, sodium hydroxide, sorbitol sorbitan solution, titanium dioxide

Questions or comments?1-800-986-0369 (Mon-Fri 9AM - 5PM EST)

Alka-Seltzer Plus® Maximum Strength Cough, Mucus & Congestion Night PowerMax® Gels

Drug Facts

Active ingredients (in each capsule) Purposes

Acetaminophen 325 mg…………….… ……...Pain reliever/fever reducer

Dextromethorphan hydrobromide 10 mg…… ………Cough suppressant

Doxylamine succinate 6.25 mg…………… ………………...Antihistamine

Phenylephrine hydrochloride 5 mg.....…… ………...Nasal decongestant

Uses

· temporarily relieves these symptoms due to a cold or flu:

· minor aches and pains · headache

· nasal and sinus congestion · cough

· sore throat · runny nose · sneezing

· temporarily reduces fever

Warnings

Liver warning: This product contains acetaminophen. Severe liver damage may occur if you take

· more than 4,000 mg of acetaminophen in 24 hours

· with other drugs containing acetaminophen

· 3 or more alcoholic drinks every day while using this product

Allergy alert: Acetaminophen may cause severe skin or severe allergic reactions. Symptoms may include:

· skin reddening · blisters · rash · hives

· facial swelling · asthma (wheezing) · shock

If a skin or general allergic reaction occurs, stop use and seek medical

help right away.

Sore throat warning: If sore throat is severe, persists for more than

2 days, is accompanied or followed by fever, headache, rash, nausea,

or vomiting, consult a doctor promptly.

Do not use to sedate children.

Do not use

● with any other drug containing acetaminophen (prescription or

nonprescription). If you are not sure whether a drug contains

acetaminophen, ask a doctor or pharmacist.

● if you are now taking a prescription monoamine oxidase inhibitor

(MAOI) (certain drugs for depression, psychiatric, or emotional

conditions, or Parkinson's disease), or for 2 weeks after stopping

the MAOI drug. If you do not know if your prescription drug contains

an MAOI, ask a doctor or pharmacist before taking this product.

● if you have ever had an allergic reaction to this product or any of its

ingredients

● in children under 12 years of age

Ask a doctor before use if you have

● liver disease ● heart disease ● high blood pressure

● thyroid disease ● diabetes ● glaucoma

● cough with excessive phlegm (mucus)

● a breathing problem such as emphysema or chronic bronchitis

● difficulty in urination due to enlargement of the prostate gland

● persistent or chronic cough such as occurs with smoking, asthma,

or emphysema

Ask a doctor or pharmacist before use if you are

● taking the blood thinning drug warfarin

● taking sedatives or tranquilizers

When using this product

● do not exceed recommended dosage

● may cause marked drowsiness

● avoid alcoholic drinks

● alcohol, sedatives, and tranquilizers may increase drowsiness

● be careful when driving a motor vehicle or operating machinery

● excitability may occur, especially in children

Stop use and ask a doctor if

· pain, cough, or nasal congestion gets worse or lasts more than

7 days

· fever gets worse or lasts more than 3 days

· redness or swelling is present

· new symptoms occur

· cough comes back or occurs with rash or headache that lasts.

These could be signs of a serious condition.

· nervousness, dizziness, or sleeplessness occurs

If pregnant or breast-feeding, ask a health professional before use.

Keep out of reach of children. In case of overdose, get medical help

or contact a Poison Control Center right away. Quick medical attention is critical for adults as well as for children even if you do not notice any signs or symptoms.

Directions

· do not take more than the recommended dose

· do not take the Day and Night products at the same time; wait 4

hours after the last Day dose before starting Night product

· adults and children 12 years and over: take 2 capsules with water

every 4 hours. Do not exceed 4 capsules in 12 hours or as

directed by a doctor.

· children under 12 years: do not use

Other information

· store at 15° - 25°C (59° - 77°F)

Inactive ingredients

Inactive ingredients D&C yellow No. 10, FD&C blue No. 1, gelatin, glycerin, polyethylene glycol, potassium aluminum silicate, povidone, propylene glycol, purified water, shellac, sodium hydroxide, sorbitol sorbitan solution, titanium dioxide

Questions or comments? 1-800-986-0369 (Mon-Fri 9AM - 5PM EST)